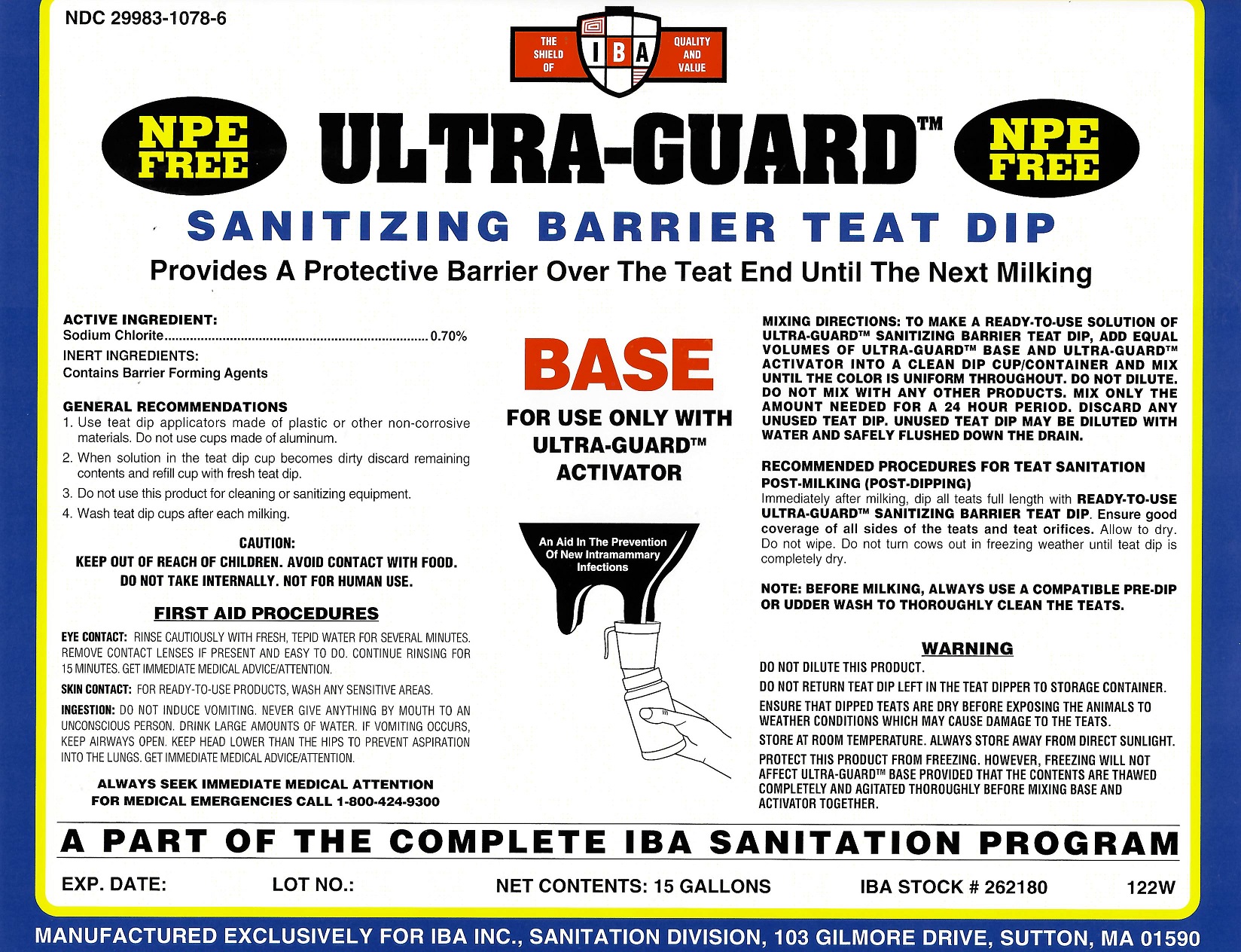 DRUG LABEL: Ultra-Guard Base
NDC: 29983-1078 | Form: LIQUID
Manufacturer: IBA
Category: animal | Type: OTC ANIMAL DRUG LABEL
Date: 20251211

ACTIVE INGREDIENTS: SODIUM CHLORITE 0.70 kg/100 kg

Ultra-Guard Base

Active Ingredient

Sodium Chlorite 0.7%

Inert Ingredients

Contains barrier forming agents

Mixing Directions

To make a ready-to-use solution of Ultra-Guard sanitizing barrier, add equal volumes of Ultra-Guard Base and Ultra-Guard Activator into a clean dip cup/container and mix until the color is uniform throughout. Do not dilute. Mix only amount needed for one milking of the herd. Discard any unused teat dip. Do not mix with any other products.

Recommended Procedures for teat dip sanitation

POST-MILKING (POST-DIPPING)
Immediately after milking, dip all teats full length with READY-TO-USE ULTRA-GUARD SANITIZING TEAT DIP. Ensure good coverage of all sides of the teats and teat orifices. Allow to dry. Do not wipe. Do not turn cows out in freezing weather until teat dip is completely dry.

NOTE: Before milking, use a compatile pre-dip or udder wash to thoroughy clean the teats.

Warning

Do not dilute this product.

Do not return teat dip left in the teat dipper to storage container.

Ensure that teat dips are dry before exposing the animals to weather conditions that may cause damage to the teats.

Protect this product from freezing. Store at room temperature. Always store away from direct sunlight.

First Aid

EYE CONTACT: Rinse cautiously with fresh, tepid water for several minutes. Remove contact lenses if present and easy to do. Continue rinsing for 15 minutes. Get immediate medical advice/attention. SKIN CONTACT: For RTU products wash any sensitive areas. INGESTION: Do not induce vomiting. Never give anything by mouth to an unconscious person. Drink large amounts of water. If vomiting occurs, keep airways open. Keep head lower than the hips to prevent aspiration into the lungs. Get immediate medical advice/attention.

Caution

Keep out of reach of children. Avoid contact with food. Do not take internally.